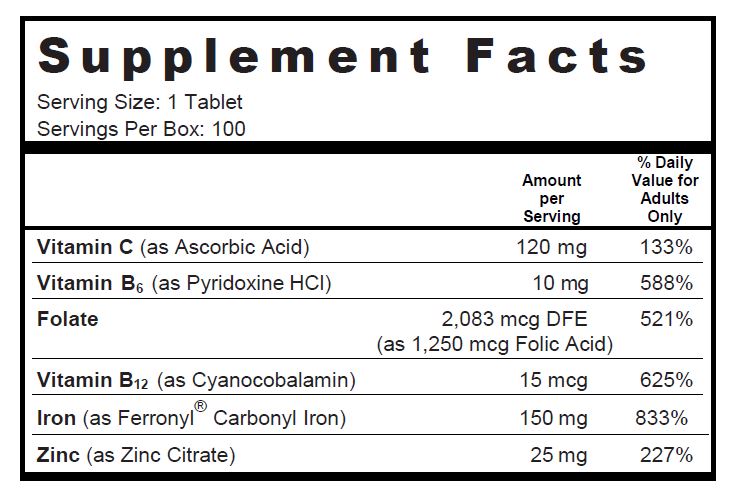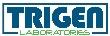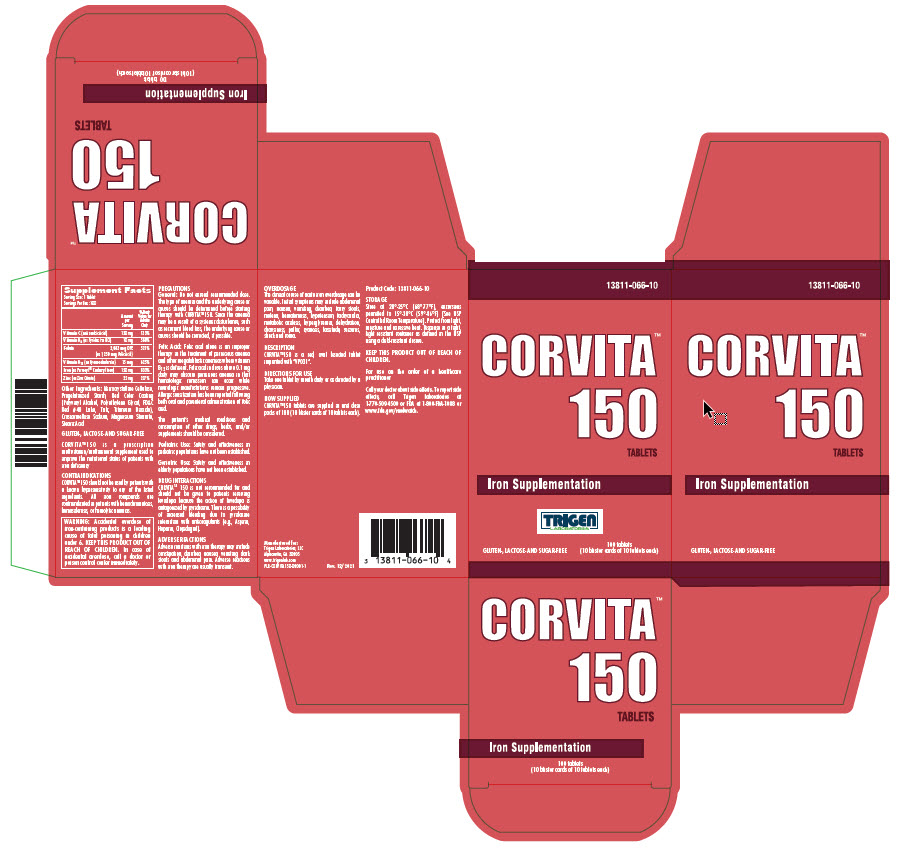 DRUG LABEL: CORVITA 150
NDC: 13811-066 | Form: TABLET
Manufacturer: Trigen Laboratories, LLC
Category: other | Type: DIETARY SUPPLEMENT
Date: 20211223

ACTIVE INGREDIENTS: Iron 150 mg/1 1; Folic Acid 1.25 mg/1 1; ascorbic acid 120 mg/1 1; pyridoxine Hydrochloride 10 mg/1 1; Cyanocobalamin 15 ug/1 1; ZINC 25 mg/1 1
INACTIVE INGREDIENTS: Cellulose, Microcrystalline; POLYVINYL ALCOHOL, UNSPECIFIED; POLYETHYLENE GLYCOL, UNSPECIFIED; FD&C RED NO. 40; TALC; TITANIUM DIOXIDE; CROSCARMELLOSE SODIUM; MAGNESIUM STEARATE; STEARIC ACID; STARCH, CORN

CORVITA TM 150 TABLETS

SUPPLEMENT FACTS

Other Ingredients: Microcrystalline Cellulose, Pregelatinized Starch, Red Color Coating (Polyvinyl Alcohol, Polyethylene Glycol, FD&C Red #40 Lake, Talc, Titanium Dioxide), Croscarmellose Sodium, Magnesium Stearate, Stearic Acid

GLUTEN-, LACTOSE- AND SUGAR-FREE

CORVITA™ 150 is a prescription multivitamin/multimineral supplement used to improve the nutritional status of patients with iron deficiency

CONTRAINDICATIONS

CORVITA™ 150 should not be used by patients with a known hypersensitivity to any of the listed ingredients. All iron compounds are contraindicated in patients with hemochromatosis, hemosiderosis, or hemolytic anemias.

WARNINGS

WARNING: Accidental overdose of iron-containing products is a leading cause of fatal poisoning in children under 6. KEEP THIS PRODUCT OUT OF REACH OF CHILDREN. In case of accidental overdose, call a doctor or poison control center immediately.

PRECAUTIONS

General: Do not exceed recommended dose. The type of anemia and the underlying cause or causes should be determined before starting therapy with CORVITA™150. Since the anemia may be a result of a systemic disturbance, such as recurrent blood loss, the underlying cause or causes should be corrected, if possible.

Folic Acid: Folic acid alone is an improper therapy in the treatment of pernicious anemia and other megaloblastic anemias where vitamin B12 is deficient. Folic acid in doses above 0.1 mg daily may obscure pernicious anemia in that hematologic remission can occur while neurologic manifestations remain progressive. Allergic sensitization has been reported following both oral and parenteral administration of folic acid.

The patient’s medical conditions and consumption of other drugs, herbs, and/or supplements should be considered.

Pediatric Use: Safety and effectiveness in pediatric populations have not been established.

Geriatric Use: Safety and effectiveness in elderly populations have not been established.

DRUG INTERACTIONS

CORVITA™150 is not recommended for and should not be given to patients receiving levodopa because the action of levodopa is antagonized by pyridoxine. There is a possibility of increased bleeding due to pyridoxine interaction with anticoagulants (e.g., Aspirin, Heparin, Clopidogrel).

ADVERSE REACTIONS

Adverse reactions with iron therapy may include constipation, diarrhea, nausea, vomiting, dark stools and abdominal pain. Adverse reactions with iron therapy are usually transient.

OVERDOSAGE

The clinical course of acute iron overdosage can be variable. Initial symptoms may include abdominal pain, nausea, vomiting, diarrhea, tarry stools, melena, hematemesis, hypotension, tachycardia, metabolic acidosis, hyperglycemia, dehydration, drowsiness, pallor, cyanosis, lassitude, seizures, shock and coma.

DESCRIPTION

CORVITA™ 150 is a red, oval bisected tablet imprinted with “VP031”.

DIRECTIONS FOR USE

Take one tablet by mouth daily or as directed by a physician.

HOW SUPPLIED

CORVITA™ 150 tablets are supplied in unit dose packs of 100 (10 blister cards of 10 tablets each).

PRODUCT CODE 13811-066-10

STORAGE

Store at 20°-25°C (68°-77°F), excursions permitted to 15°-30°C (59°-86°F) [See USP Controlled Room Temperature]. Protect from light and moisture and avoid excessive heat. Dispense in a tight, light resistant container as defined in the USP using a child-resistant closure.

HEALTH CLAIM

KEEP THIS PRODUCT OUT OF REACH OF CHILDREN.

For use on the order of a healthcare practitioner

Call your doctor about side effects. To report side effects, call Trigen Laboratories at 1-770-509-4500 or FDA at 1-800-FDA-1088 or www.fda.gov/medwatch.

PLR-CORVITA150-00001-1 Rev. 12/2021

Manufactured for:
Trigen Laboratories, LLC
Alpharetta, GA 30005

www.trigenlab.com

PRINCIPAL DISPLAY PANEL - 100 Tablets Blister Label

13811-066-10

CORVITA TM 150
TABLETS

Iron Supplementation

Gluten-, Lactose-, and Sugar-Free